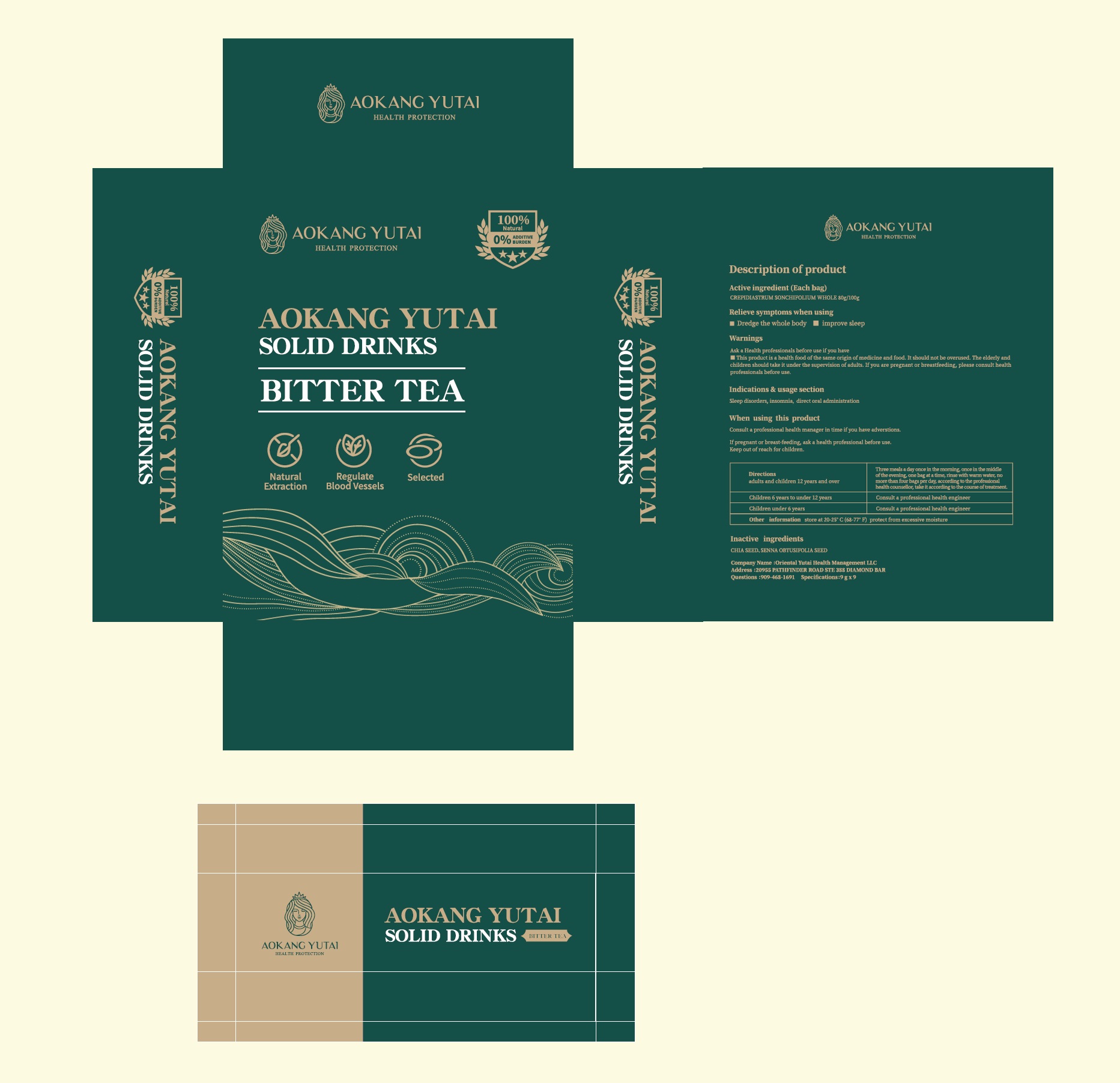 DRUG LABEL: Ixeris Denticulata
NDC: 83494-001 | Form: POWDER
Manufacturer: Oriental Yutai Health Management LLC
Category: homeopathic | Type: HUMAN OTC DRUG LABEL
Date: 20230526

ACTIVE INGREDIENTS: CREPIDIASTRUM SONCHIFOLIUM WHOLE 80 g/100 g
INACTIVE INGREDIENTS: CHIA SEED; SENNA OBTUSIFOLIA SEED

Active ingredients

Lactuca indica

Purpose

Unclog the whole body and improve sleep

Indications & usage section

Sleep disorders, insomnia， direct oral administration

Warnings

Ask a Health professionals before use if you have

■This product is a health food of the same origin of medicine and food. It should not be overused. The elderly and children should take it under the supervision of adults. If you are pregnant or breastfeeding, please consult health professionals before use.

Keep out of reach for children.

When using this product

Consult a professional health manager in time if you have adverstions.
If pregnant or breast-feeding, ask a health professional before use.

Directions

adults and children 12 years and over Three meals a day once in the morning, once in the middle of the evening, one bag at a time, rinse with warm water, no more than four bags per day, according to the professional health counsellor, take it according to the course of treatment.
children 6 years to under 12 years Consult a professional health engineer
children under 6 years Consult a professional health engineer

Inactive ingredients

CHIA SEED、SENNA OBTUSIFOLIA SEED